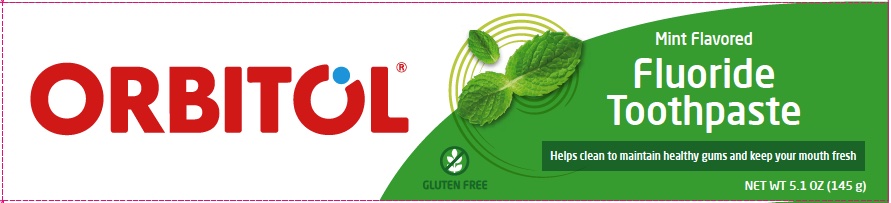 DRUG LABEL: Orbitol Mint Flavored Fluoride Toothpaste
NDC: 62685-231 | Form: PASTE
Manufacturer: tropical degil cosmetics industries ltd
Category: otc | Type: HUMAN OTC DRUG LABEL
Date: 20240310

ACTIVE INGREDIENTS: SODIUM MONOFLUOROPHOSPHATE 1.1 g/100 g
INACTIVE INGREDIENTS: LIMONENE, (+)-; CALCIUM CARBONATE; SILICON DIOXIDE; SACCHARIN SODIUM; SODIUM BENZOATE; BENZOIC ACID; SODIUM LAURYL SULFATE; WATER; SORBITOL; CARBOXYMETHYLCELLULOSE SODIUM

Orbitol Mint Flavored Fluoride Toothpaste

Active ingredient

Sodium monofluorophosphate 1.1% w/w (1450 ppm fluoride ion)

Purpose

Anticavity

Use

Aids in the prevention of dental cavities

WARNINGS

Do not use if you are sensitive to any of the ingredients in this prouduct.

When using this product avoid contact with eyes.

Keep out of reach of children under 6 years of age. If more than used for brushing is accidentally swallowed, get medical help or contact a Poison Control Center right away.

Directions

- Adults and children 6 years of age and older: Brush teeth thoroughly, preferrably after each meal or at least twice a day, or as directed by a dentist or doctor. Instruct children under 12 years of age in good brushing and rinsing habits (to minimize swallowing). Supervise children as necessary until capable of using without supervision.
- Children under 6 years of age: Do not use unless directed by a dentist or doctor.

Inactive ingredients

sorbitol, water, calcium carbonate, silica, cellulose gum, sodium lauryl sulfate, flavor, sodium saccharin, sodium benzoate, benzoic acid, limonene.

Other information

Other information store below 30°C (86°F).